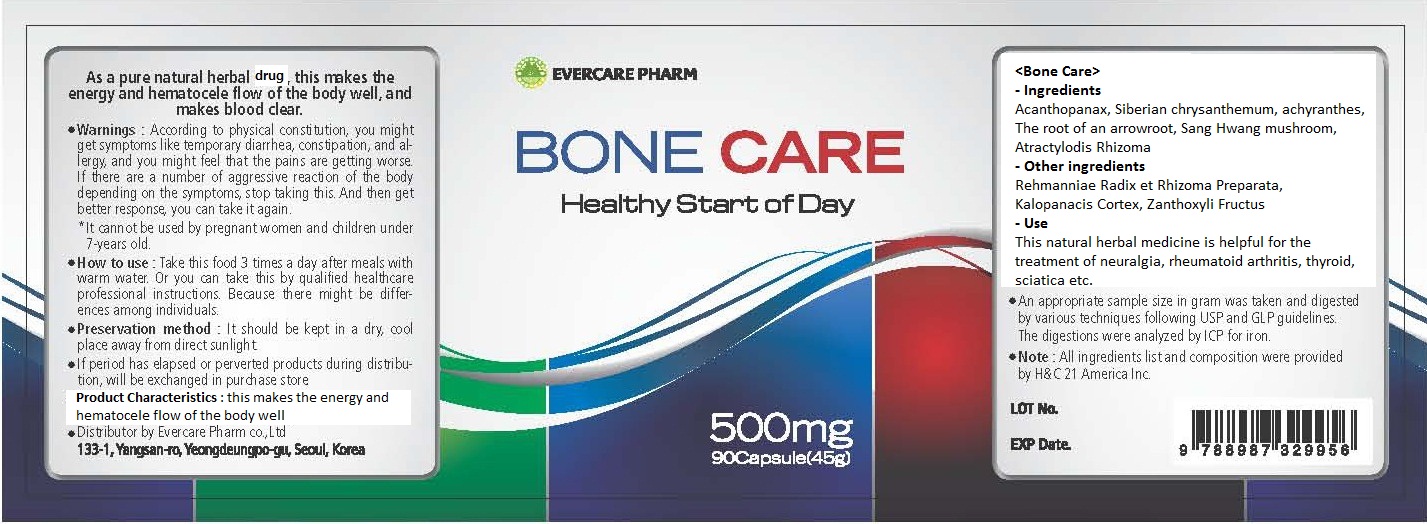 DRUG LABEL: Bone Care
NDC: 42469-1001 | Form: TABLET
Manufacturer: Evercarepharm Co., Ltd
Category: otc | Type: HUMAN OTC DRUG LABEL
Date: 20120606

ACTIVE INGREDIENTS: ATRACTYLODES LANCEA ROOT 170 mg/1 1
INACTIVE INGREDIENTS: PUERARIA MONTANA VAR. LOBATA ROOT; REHMANNIA GLUTINOSA ROOT; KALOPANAX SEPTEMLOBUS BARK; ZANTHOXYLUM SCHINIFOLIUM WHOLE; ELEUTHEROCOCCUS SESSILIFLORUS WHOLE; ACHYRANTHES JAPONICA WHOLE; PHELLINUS LINTEUS WHOLE

Drug Facts

active ingredient: atractylodis rhizoma

inactive ingredient: siberian chrysanthemum, puerariae radix, rehmanniae radix et rhizoma preparata, kalopnacis cortex, zanthoxyli fructus, acanthopanax root bark, achyranthis radix, phellinus linteus teng

PURPOSE

helpful for the treatment of neuralgia, rheumatoid arthritis, thyroid, sciatica

keep out of reach of the children

INDICATIONS AND USAGE

take 3 times a day after meals with warm water

WARNINGS

keep in a dry, cool place
keep away from direct sunlight

DOSAGE AND ADMINISTRATION

do not take if you are pregnant